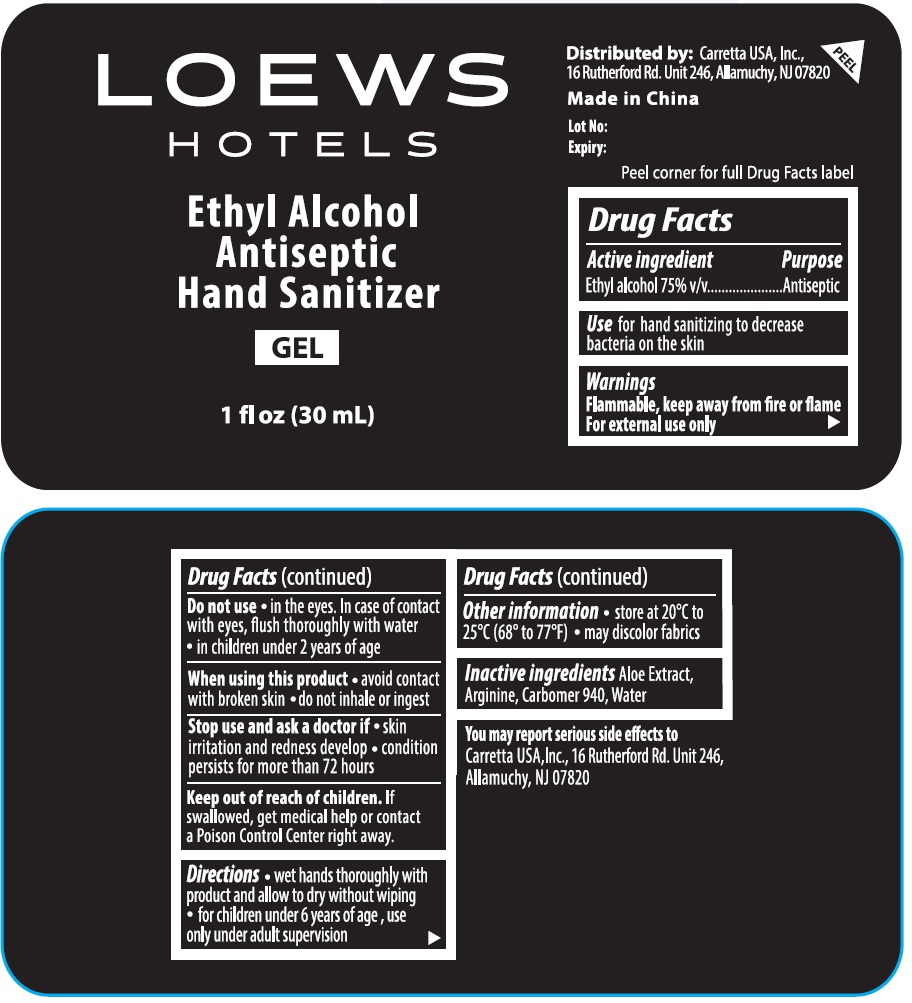 DRUG LABEL: LOEWS HOTELS Antiseptic Hand Sanitizer
NDC: 78828-222 | Form: GEL
Manufacturer: Carretta USA, Inc
Category: otc | Type: HUMAN OTC DRUG LABEL
Date: 20241231

ACTIVE INGREDIENTS: ALCOHOL 75 mL/100 mL
INACTIVE INGREDIENTS: ALOE; ARGININE; CARBOMER HOMOPOLYMER TYPE C (ALLYL PENTAERYTHRITOL CROSSLINKED); WATER

LOEWS HOTELS Ethyl Alcohol Antiseptic Hand Sanitizer GEL

Active ingredient

Ethyl alcohol 75% v/v

Purpose

Antiseptic

Use

for hand sanitizing to decrease bacteria on the skin

Warnings

Flammable, keep away from fire or flame
For external use only

Do not use • in the eyes. In case of contact with eyes, flush thoroughly with water • in children under 2 years of age

When using this product • avoid contact with broken skin • do not inhale or ingest

Stop use and ask a doctor if • skin irritation and redness develop • condition persists for more than 72 hours

Keep out of reach of children. If swallowed, get medical help or contact a Poison Control Center right away.

Directions

• wet hands thoroughly with product and allow to dry without wiping • for children under 6 years of age , use only under adult supervision

Other information

• store at 20°C to 25°C (68° to 77°F) • may discolor fabrics

Inactive ingredients

Aloe Extract, Arginine, Carbomer 940, Water

Distributed by: Carretta USA, Inc.,
16 Rutherford Rd. Unit 246, Allamuchy, NJ 07820

Made in China

Peel corner for full Drug Facts label

You may report serious side effects to
Carretta USA,Inc., 16 Rutherford Rd. Unit 246,Allamuchy, NJ 07820